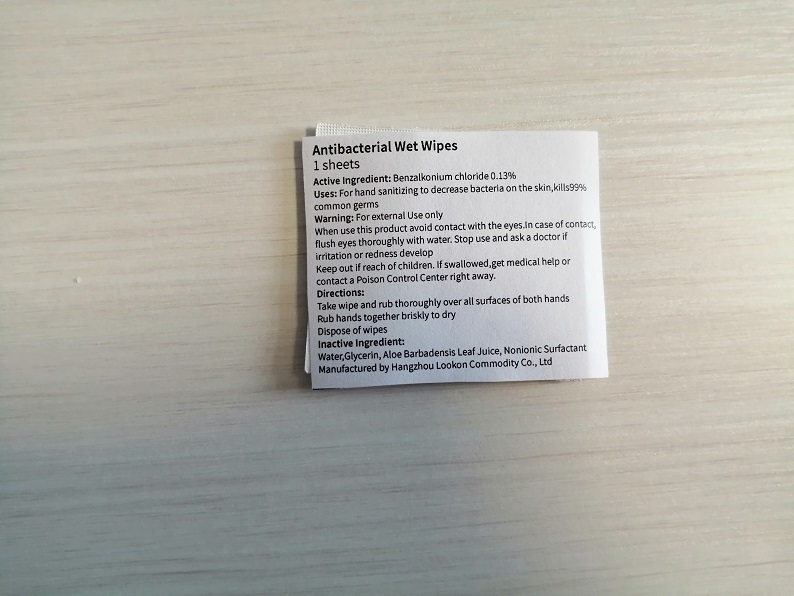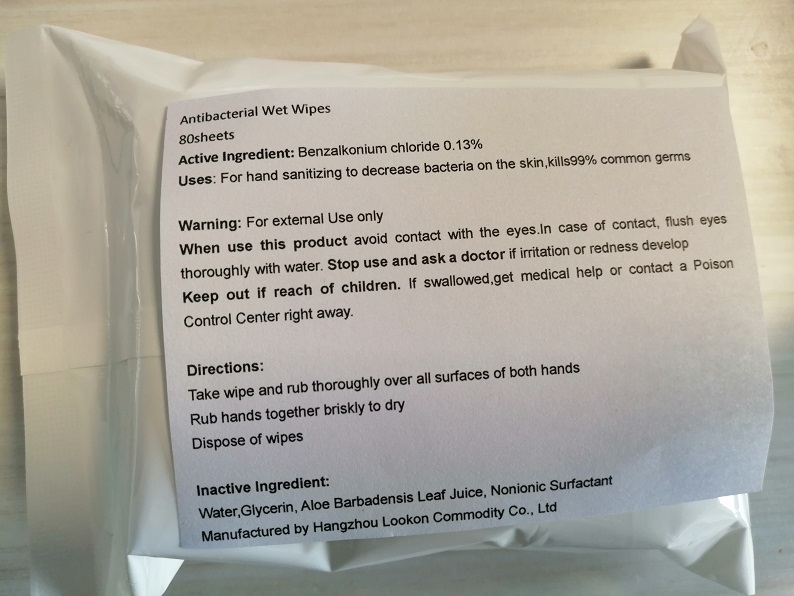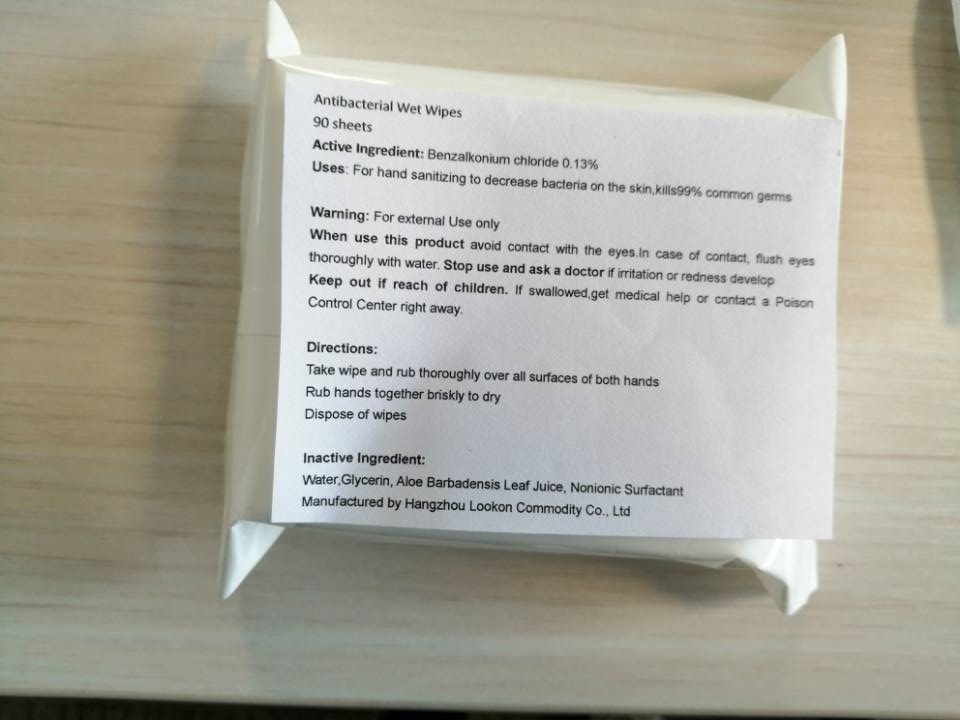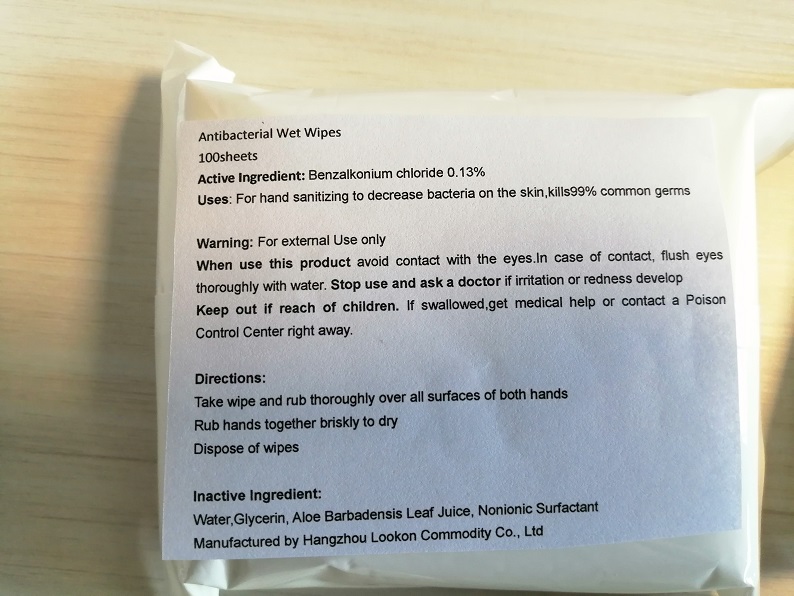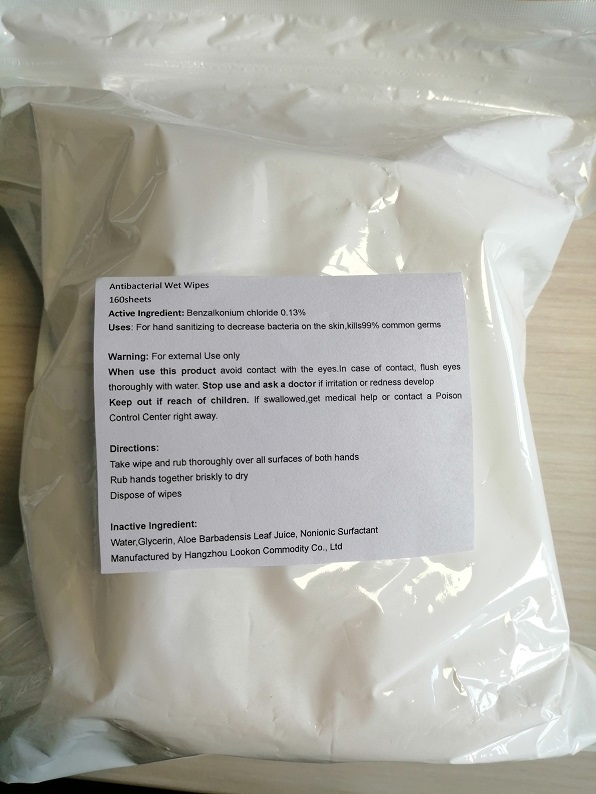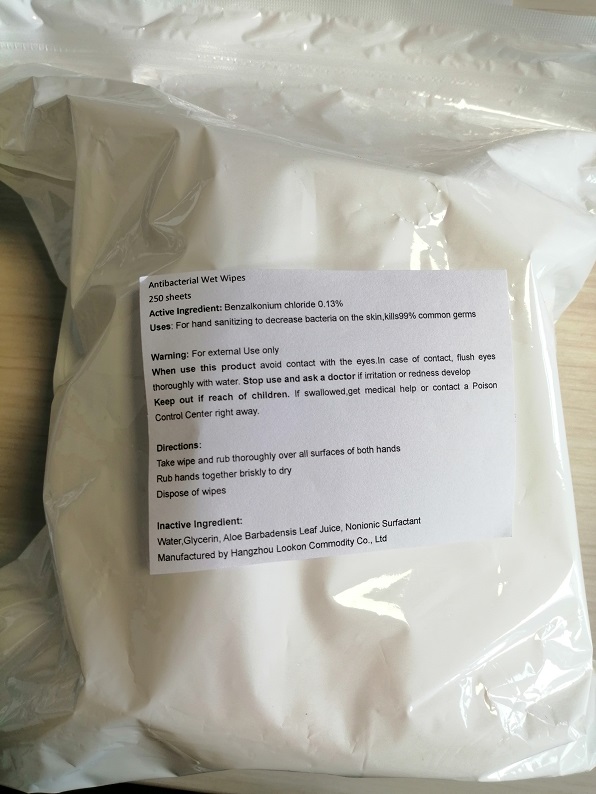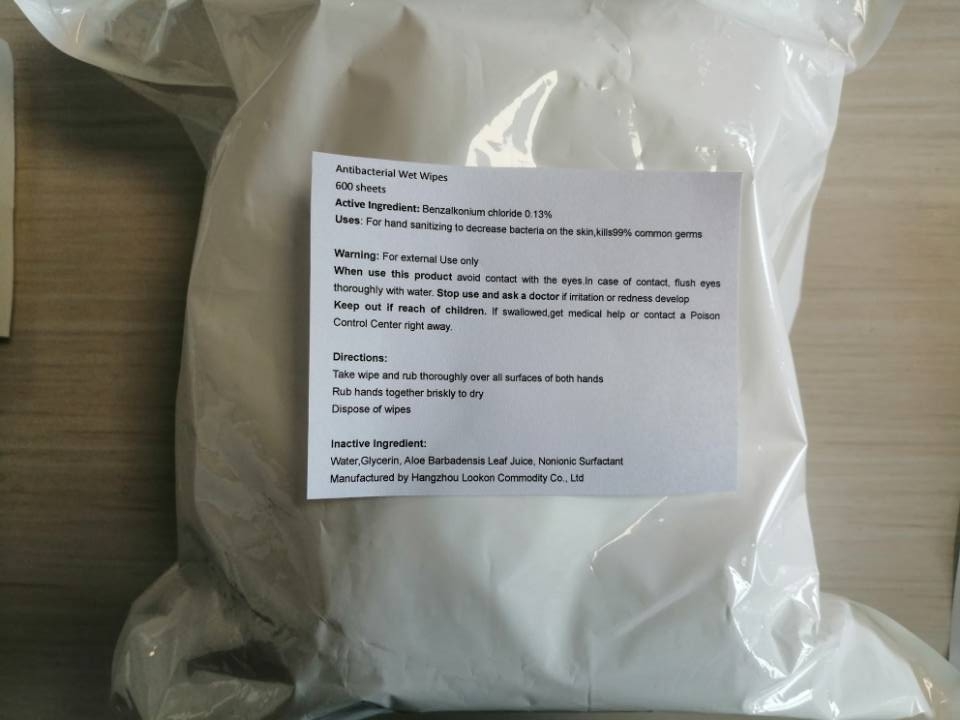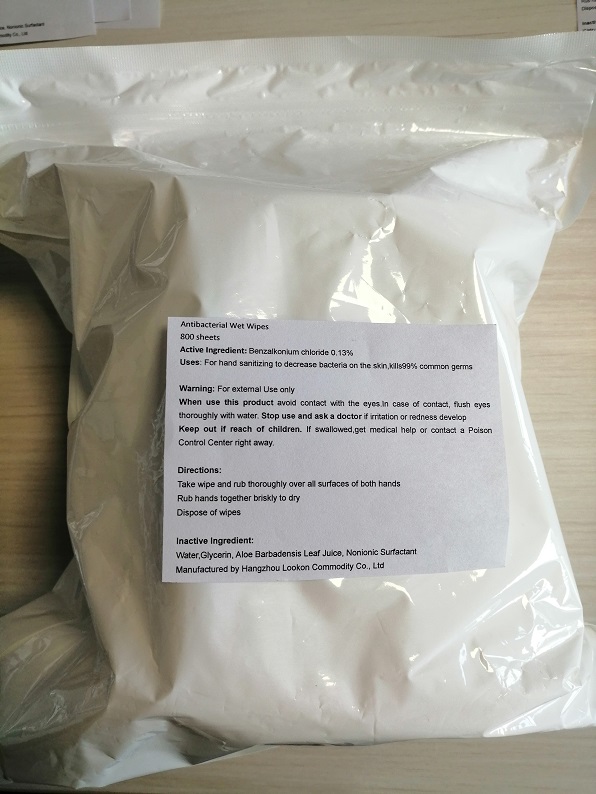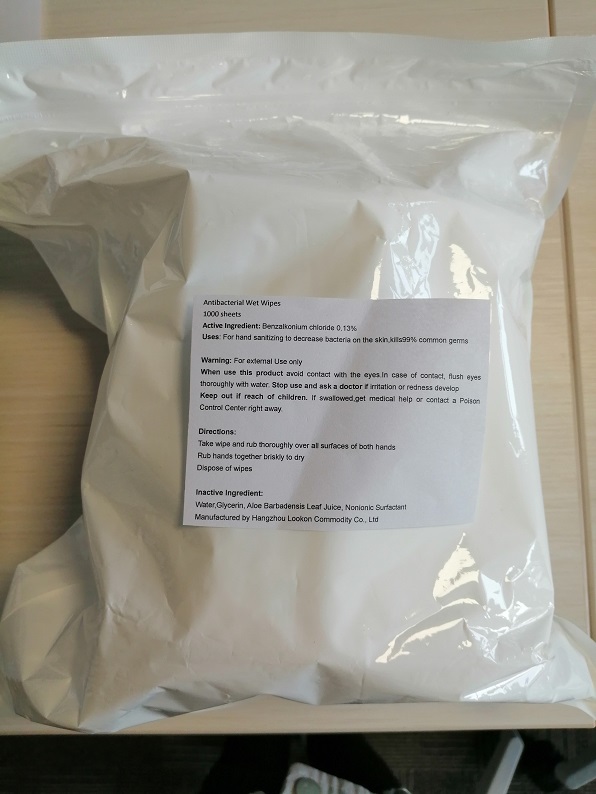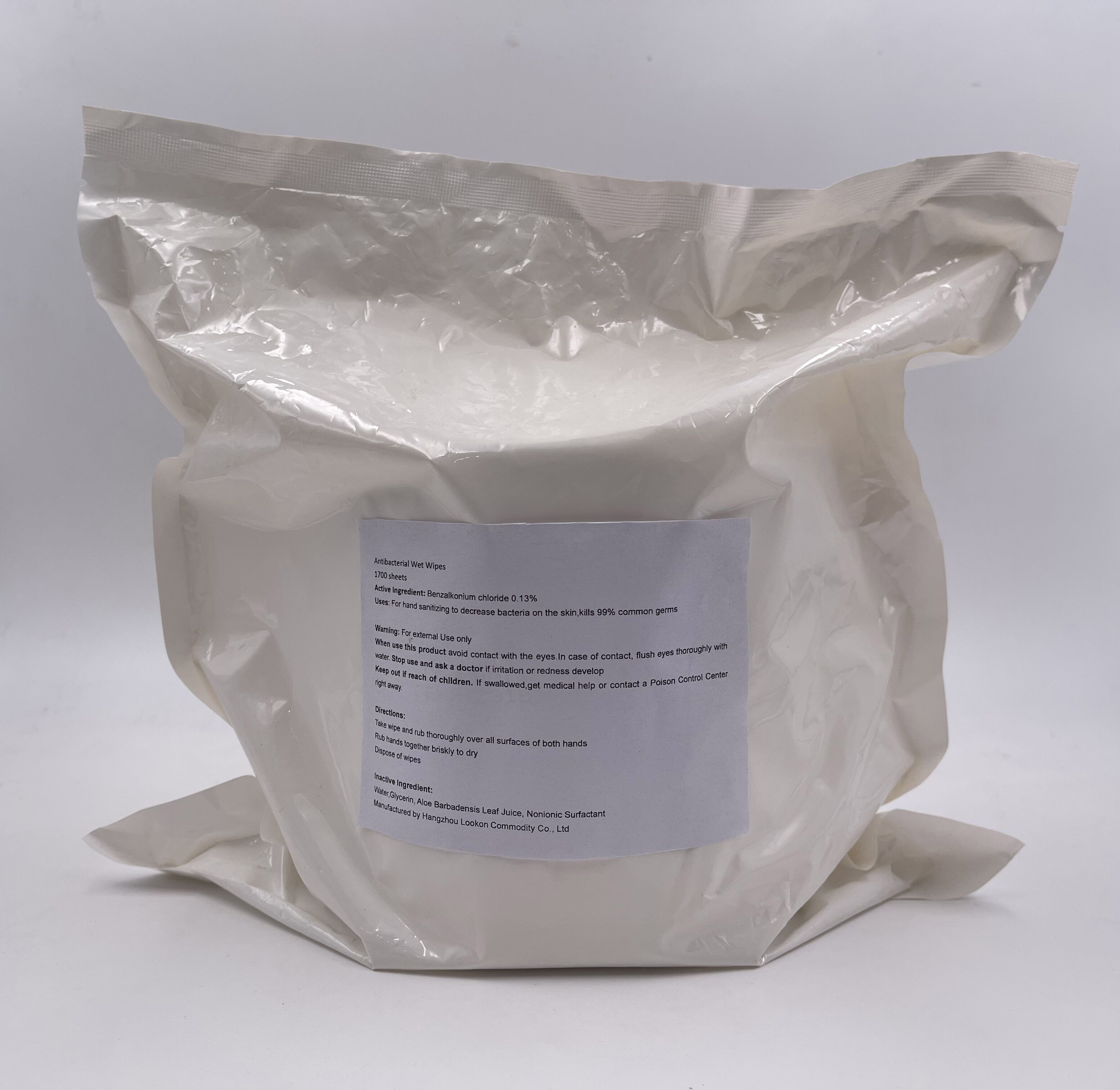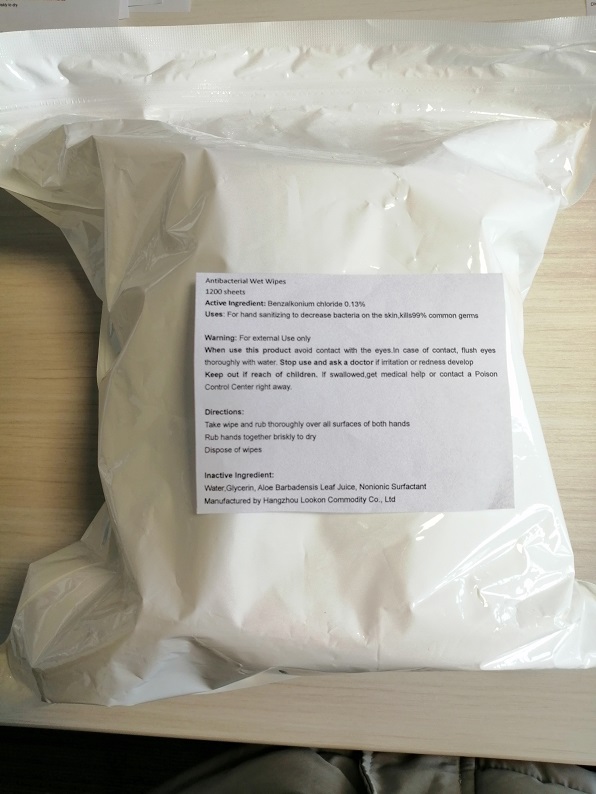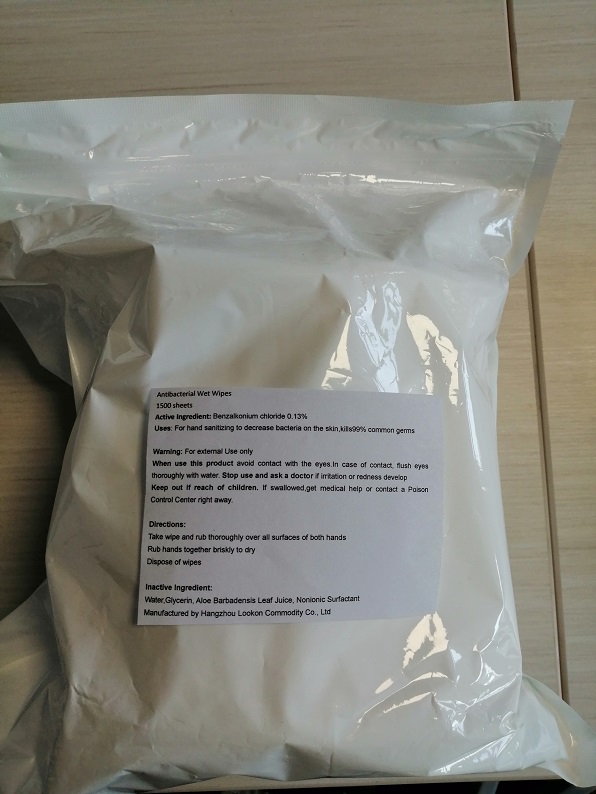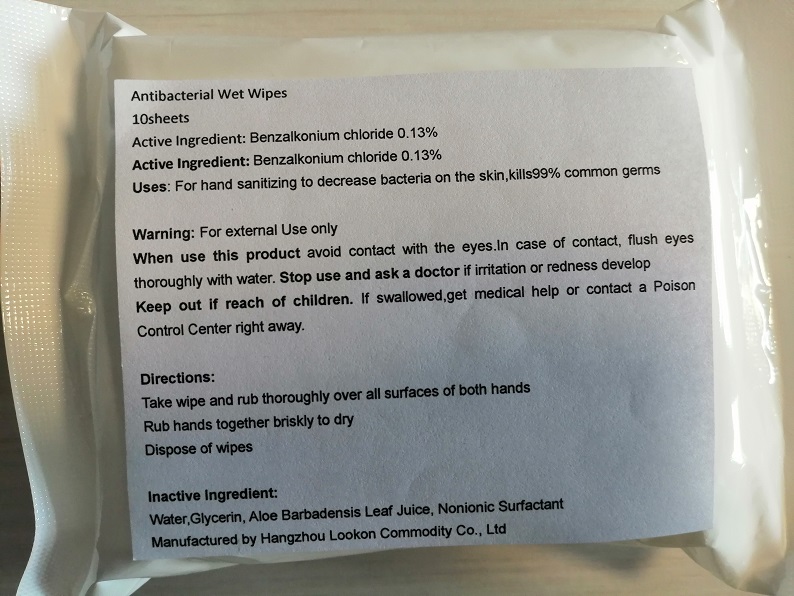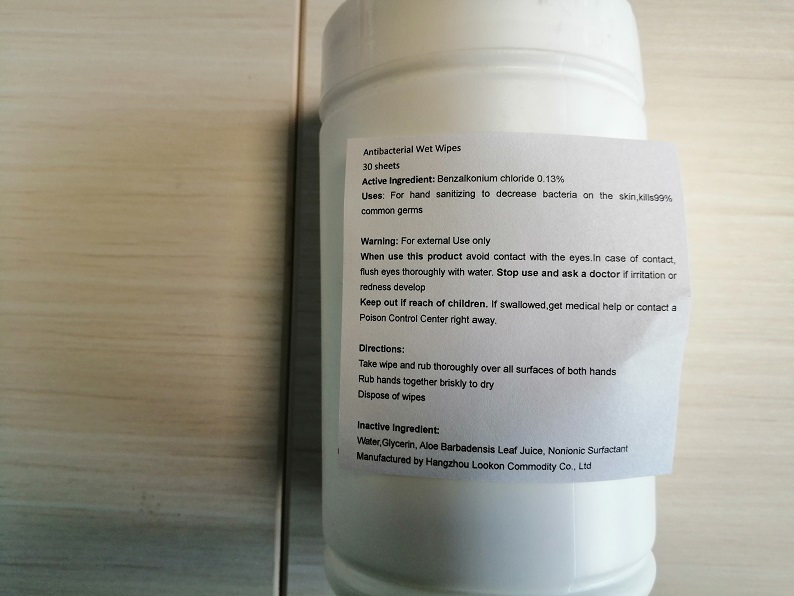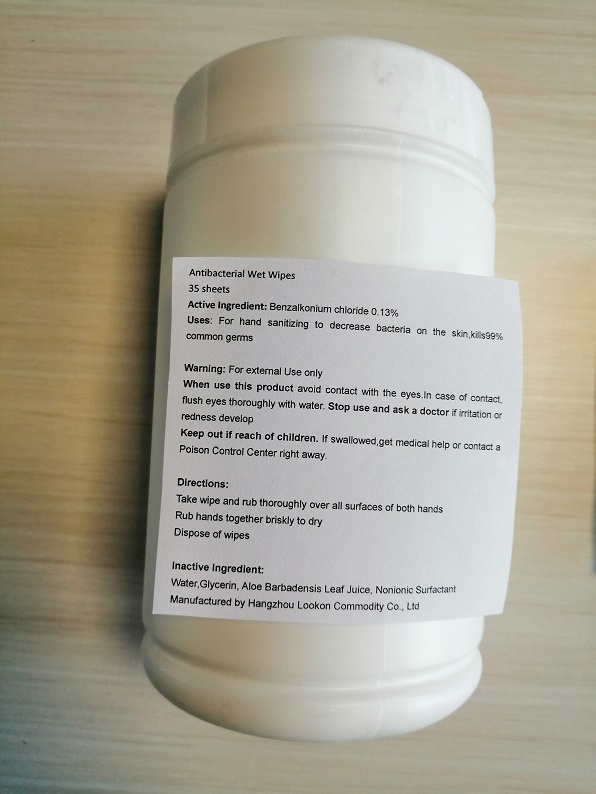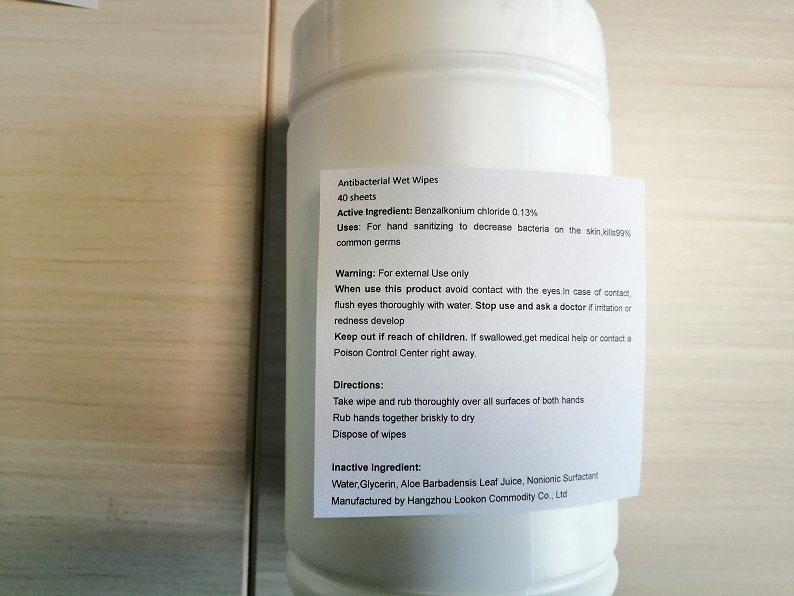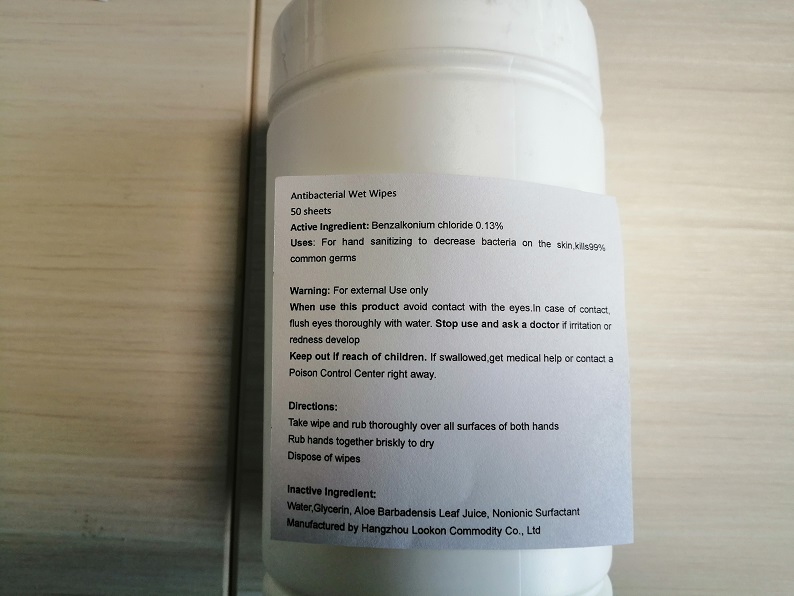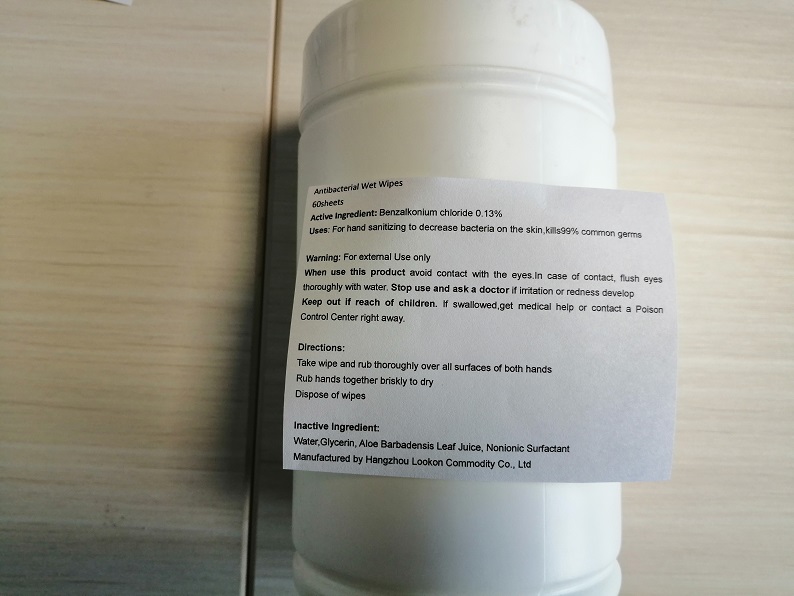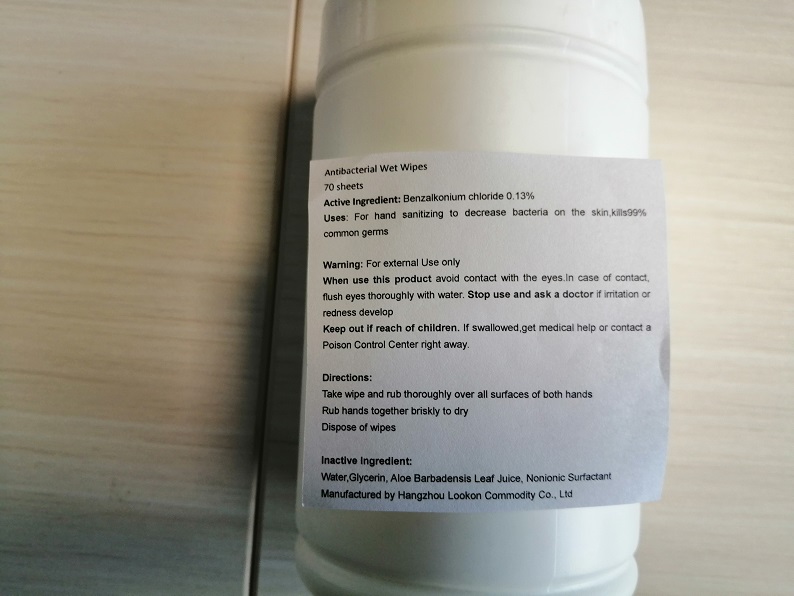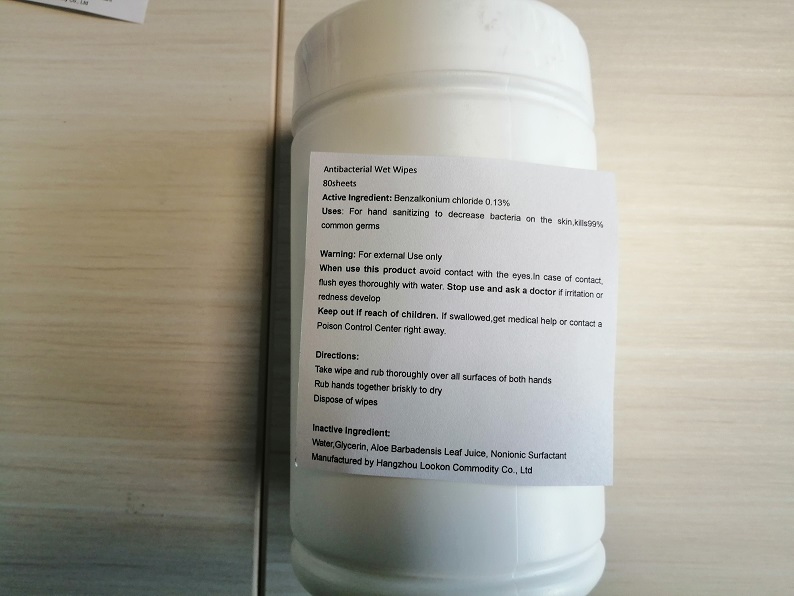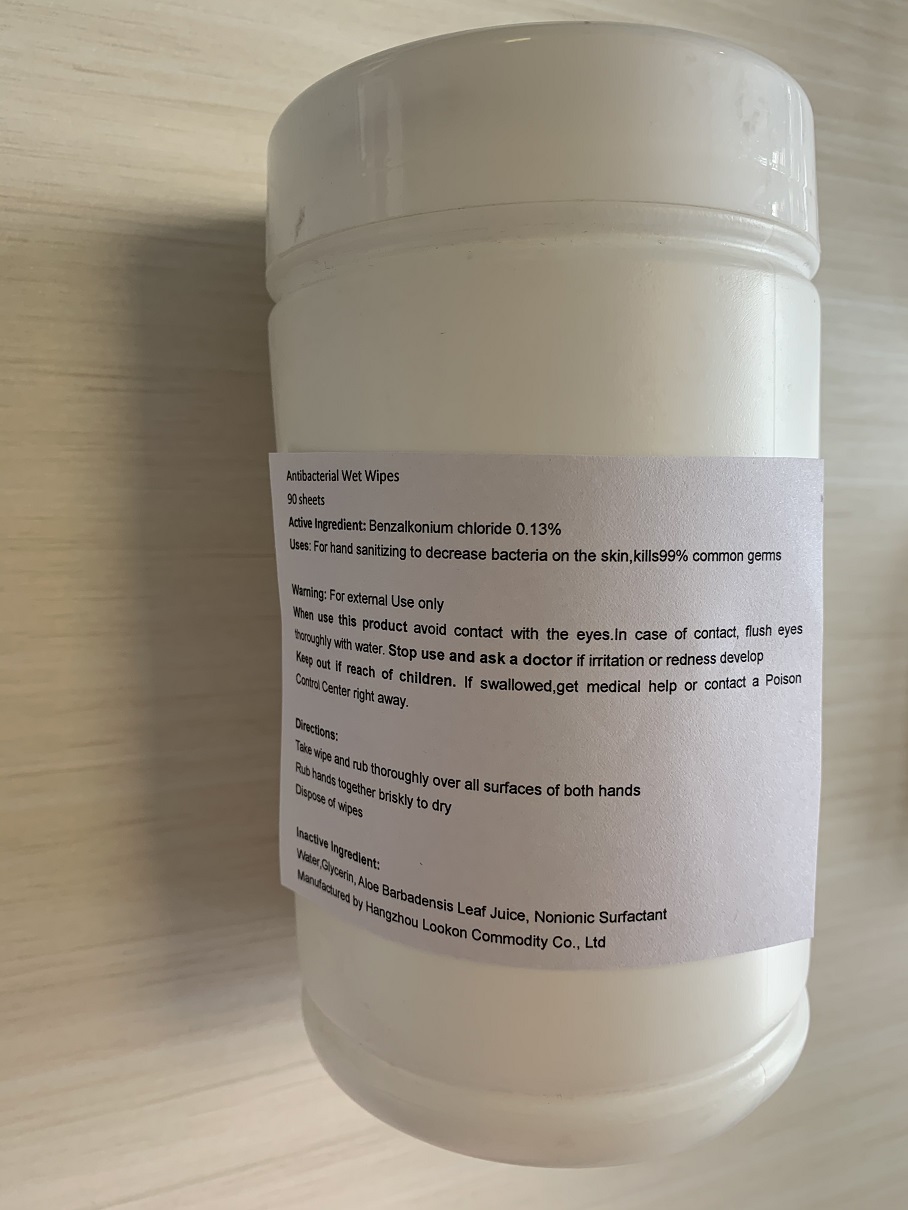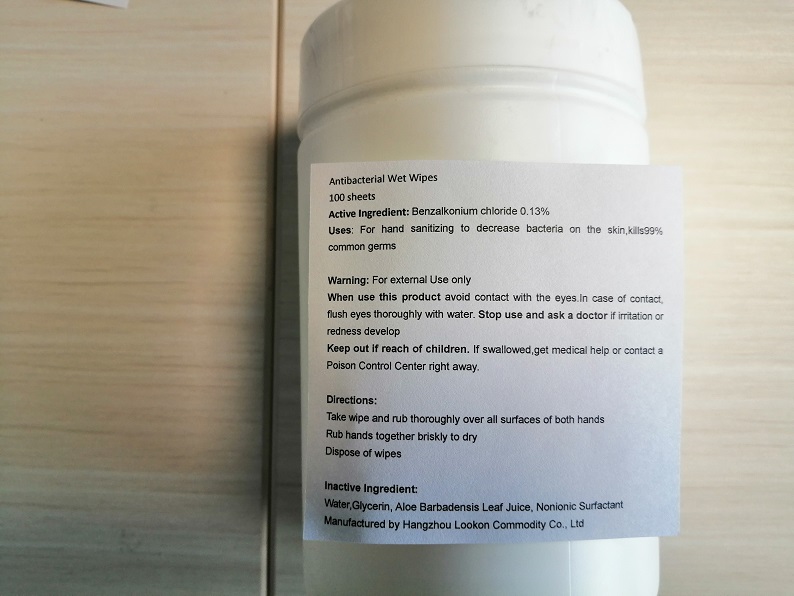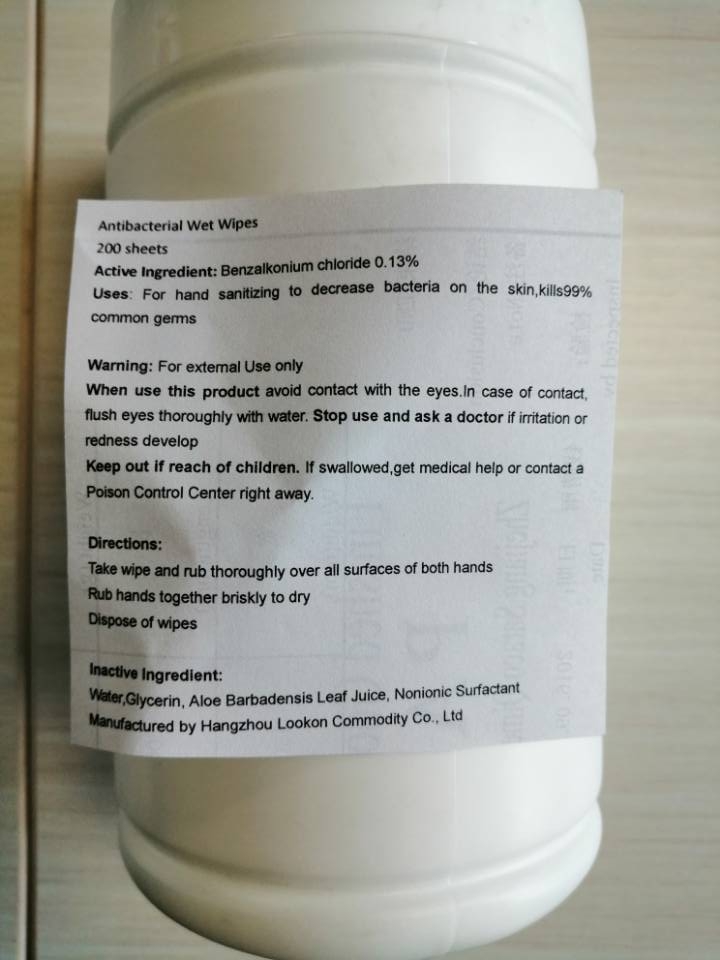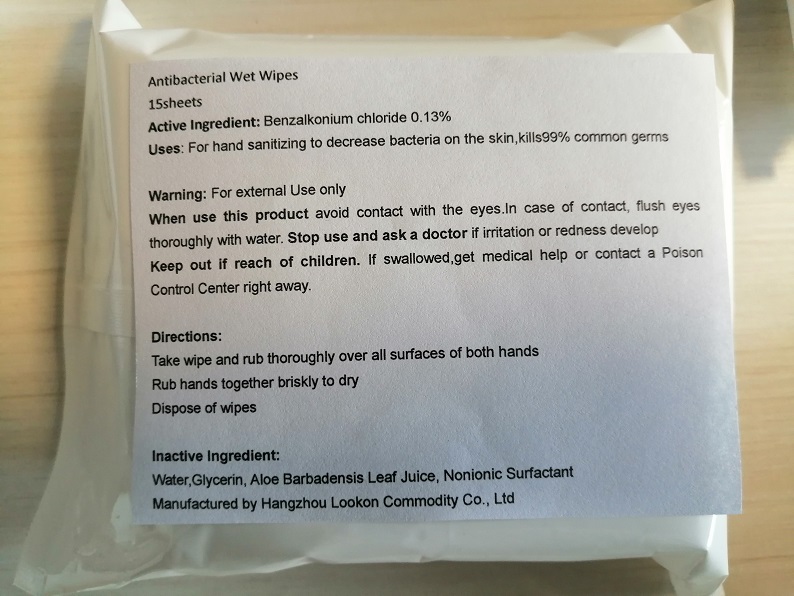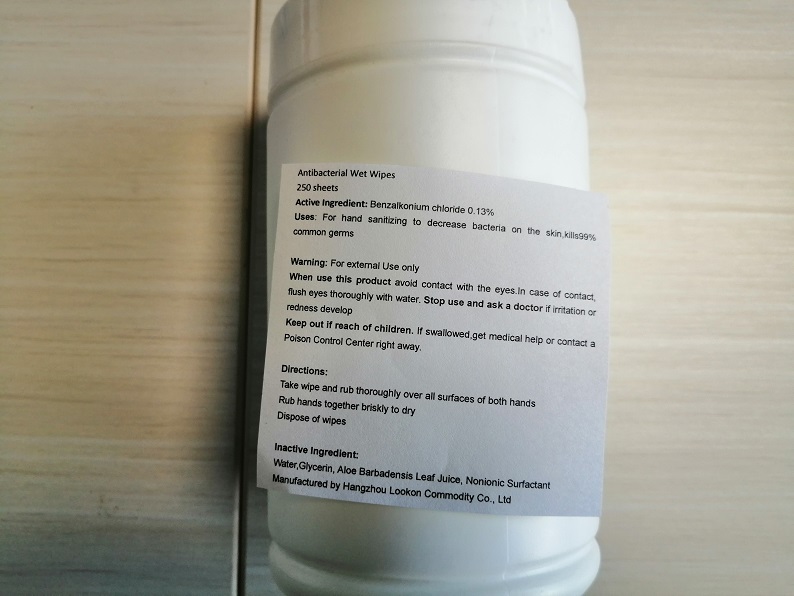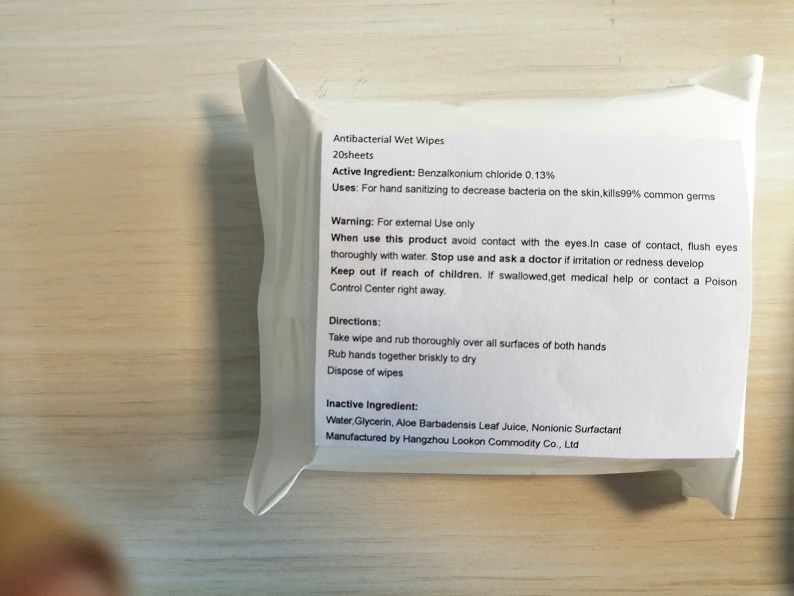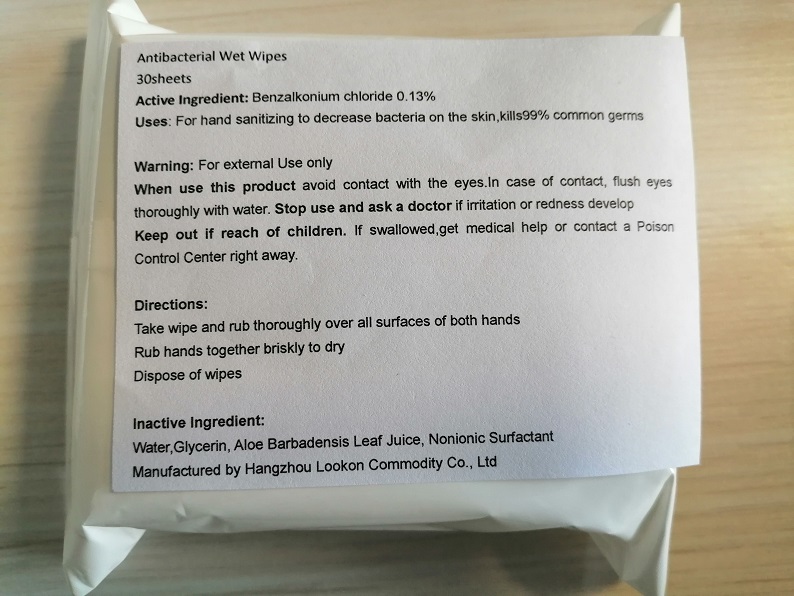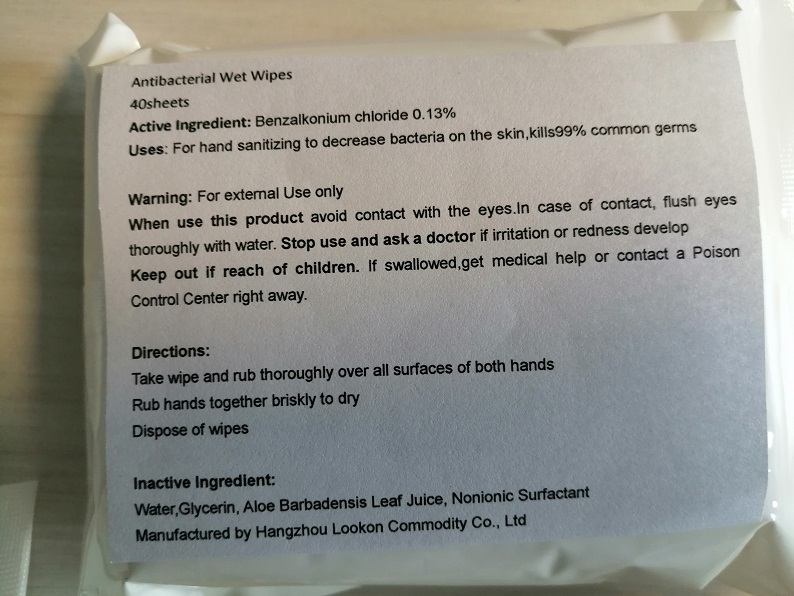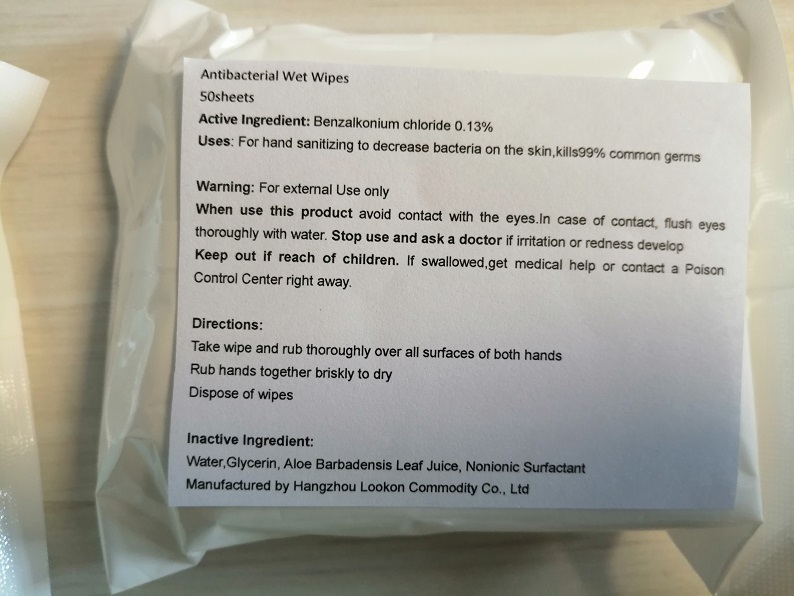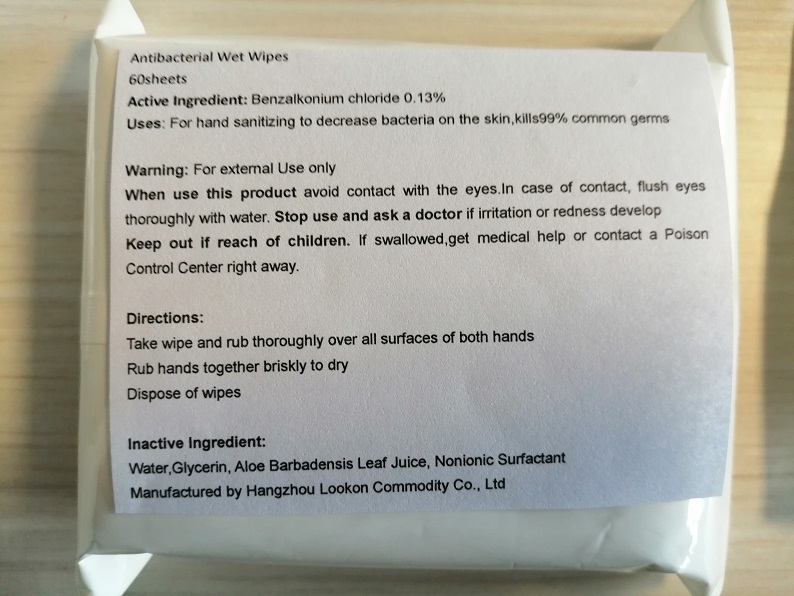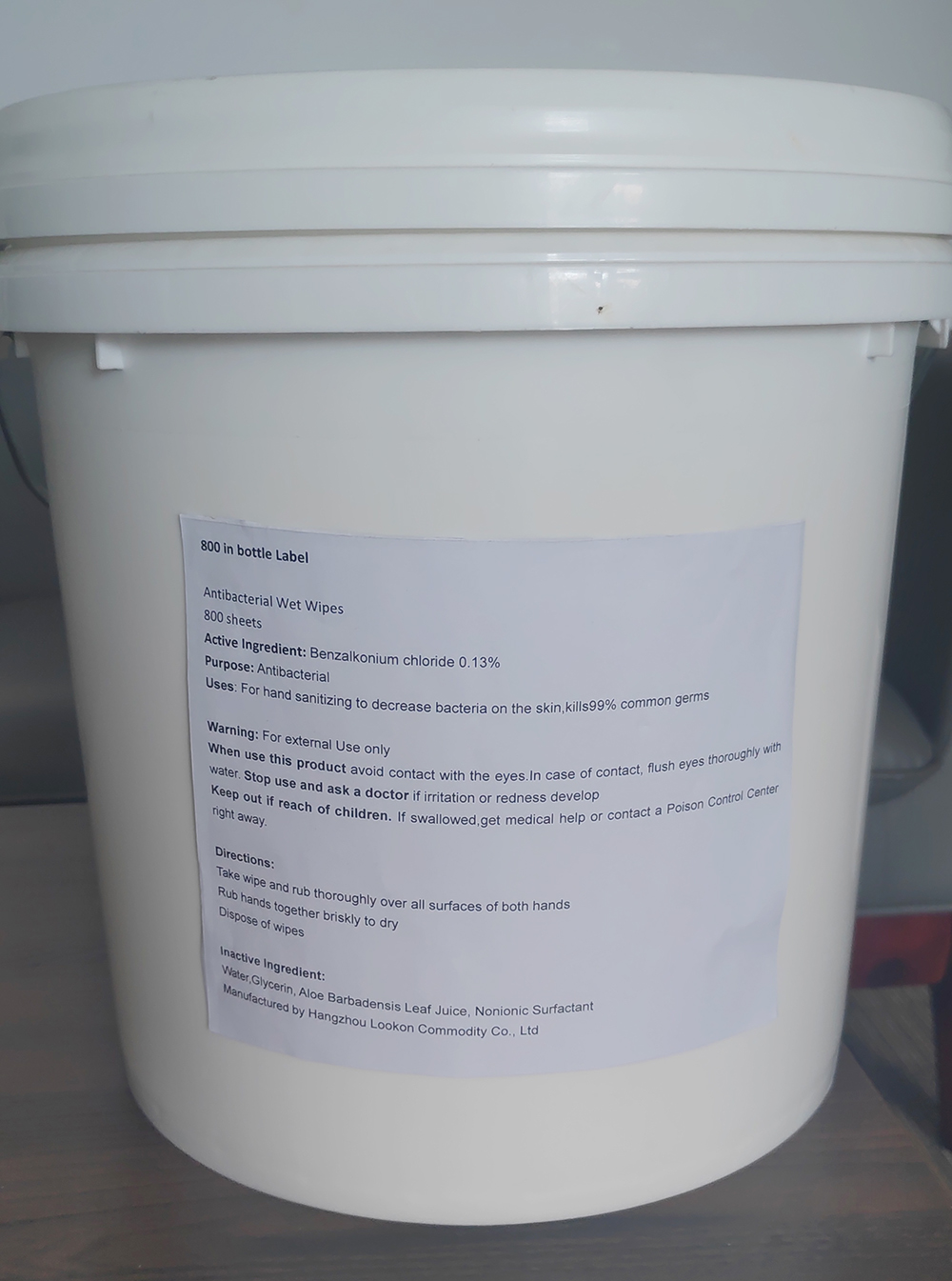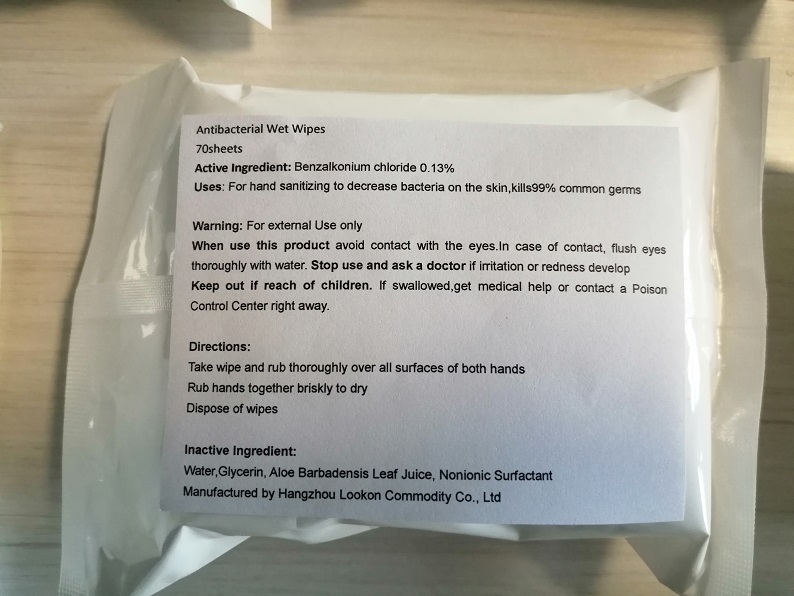 DRUG LABEL: Antibacterial Wet Wipes
NDC: 74835-004 | Form: CLOTH
Manufacturer: Hangzhou Lookon Commodity Co., Ltd
Category: otc | Type: HUMAN OTC DRUG LABEL
Date: 20210831

ACTIVE INGREDIENTS: BENZALKONIUM CHLORIDE 0.0013 1/1 1
INACTIVE INGREDIENTS: GLYCERIN; ALOE VERA LEAF; DECYL GLUCOSIDE; WATER

Antibacterial Wet Wipes

Active Ingredient

Benzalkonium chloride 0.13%

Purpose

Antibacterial Wet Wipes

Uses

For hand sanitizing to decrease bacteria on the skin,kills99% common germs

Warning

For external Use only

When use this product avoid contact with the eyes.In case of contact, flush eyes thoroughly with water.

Stop use

Stop use and ask a doctor if irritation or redness develop

Keep out of reach of children. If swallowed,get medical help or contact a Poison Control Center right away.

Directions

Take wipe and rub thoroughly over all surfaces of both hands

Rub hands together briskly to dry

Dispose of wipes

Inactive Ingredient

Water,Glycerin, Aloe Barbadensis Leaf Juice, Nonionic Surfactant

Package Label

Antibacterial Wet Wipes

1 sheets

NDC: 74835-004-01

Antibacterial Wet Wipes

10sheets

NDC: 74835-004-02

Antibacterial Wet Wipes

15sheets

NDC: 74835-004-03

Antibacterial Wet Wipes

20sheets

NDC: 74835-004-04

Antibacterial Wet Wipes

30sheets

NDC: 74835-004-05

Antibacterial Wet Wipes

40sheets

NDC: 74835-004-06

Antibacterial Wet Wipes

50sheets

NDC: 74835-004-07

Antibacterial Wet Wipes

60sheets

NDC: 74835-004-08

Antibacterial Wet Wipes

70sheets

NDC: 74835-004-09

Antibacterial Wet Wipes

80sheets

NDC: 74835-004-10

Antibacterial Wet Wipes

90sheets

NDC: 74835-004-11

Antibacterial Wet Wipes

100sheets

NDC: 74835-004-12

Antibacterial Wet Wipes

160sheets

NDC: 74835-004-13

Antibacterial Wet Wipes

250sheets

NDC: 74835-004-14

Antibacterial Wet Wipes

600sheets

NDC: 74835-004-15

Antibacterial Wet Wipes

800sheets

NDC: 74835-004-16

Antibacterial Wet Wipes

1000sheets

NDC: 74835-004-17

Antibacterial Wet Wipes

1200sheets

NDC: 74835-004-18

Antibacterial Wet Wipes

1500sheets

NDC: 74835-004-19

Bottle Package Label

Antibacterial Wet Wipes

30 sheets

NDC: 74835-004-20

Antibacterial Wet Wipes

35 sheets

NDC: 74835-004-21

Antibacterial Wet Wipes

40 sheets

NDC: 74835-004-22

Antibacterial Wet Wipes

50 sheets

NDC: 74835-004-23

Antibacterial Wet Wipes

60 sheets

NDC: 74835-004-24

Antibacterial Wet Wipes

70 sheets

NDC: 74835-004-25

Antibacterial Wet Wipes

80 sheets

NDC: 74835-004-26

Antibacterial Wet Wipes

90 sheets

NDC: 74835-004-27

Antibacterial Wet Wipes

100 sheets

NDC: 74835-004-28

Antibacterial Wet Wipes

200 sheets

NDC: 74835-004-29

Antibacterial Wet Wipes

250 sheets

NDC: 74835-004-30

Antibacterial Wet Wipes

800 sheets

NDC: 74835-004-31

PACKAGE LABEL

Antibacterial Wet Wipes

1700 sheets

NDC: 74835-004-32